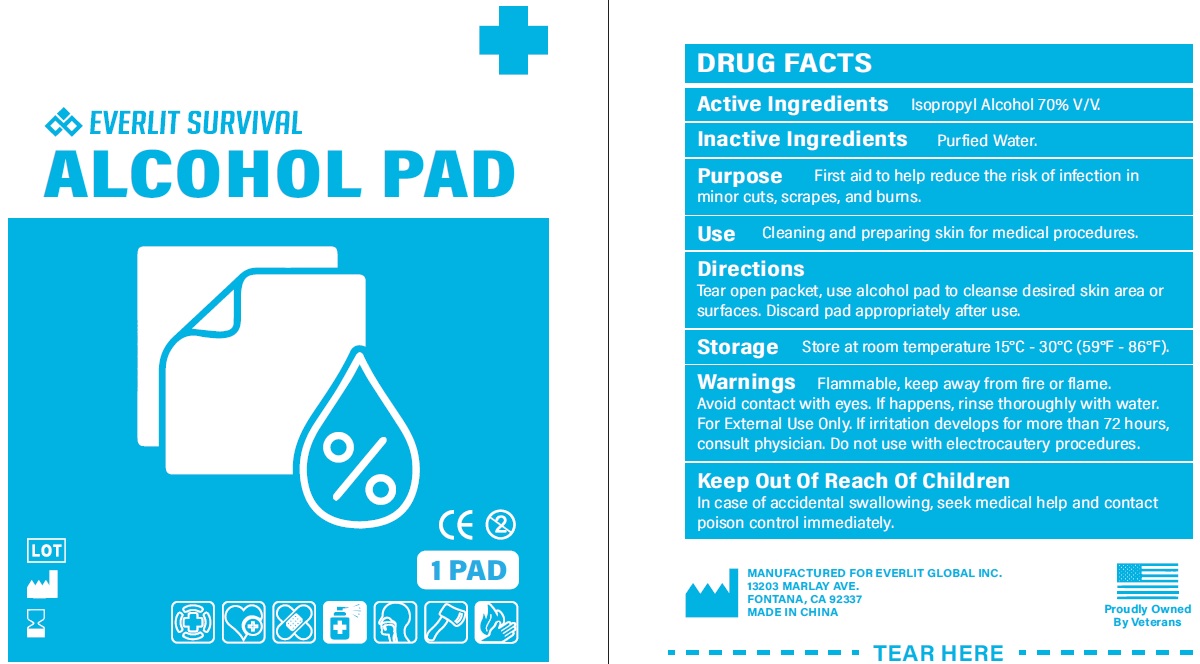 DRUG LABEL: Alcohol Pad
NDC: 72459-014 | Form: SOLUTION
Manufacturer: Yiwu Ori-Power Medtech Co.,Ltd.
Category: otc | Type: HUMAN OTC DRUG LABEL
Date: 20260101

ACTIVE INGREDIENTS: ISOPROPYL ALCOHOL 70 mL/100 mL
INACTIVE INGREDIENTS: WATER

EVERLIT SURVIVAL ALCOHOL PAD

Active Ingredients

Isopropyl Alcohol 70%v/v.

Purpose

First aid to help reduce the risk of infection in minor cuts, scrapes, and burns.

Inactive Ingredients

Purified Water.

Use

Cleaning and preparing skin for medical procedures.

Directions

Tear open packet, use alcohol pad to cleanse desired skin area or surfaces. Discard pad appropriately after use.

Storage

Store at room temperature 15°C-30°C (59°F-56°F).

Warnings

Flammable, keep away from fire or flame. Avoid contact with eyes. If happens, rinse thoroughly with water. For External Use Only. If irritation develops for more than 72 hours, consult physician.

Do not use

with electocautery procedures.

Keep Out Of Reach Of Children

In case of accidental swallowing, seek medical help and contact poison control immediately.